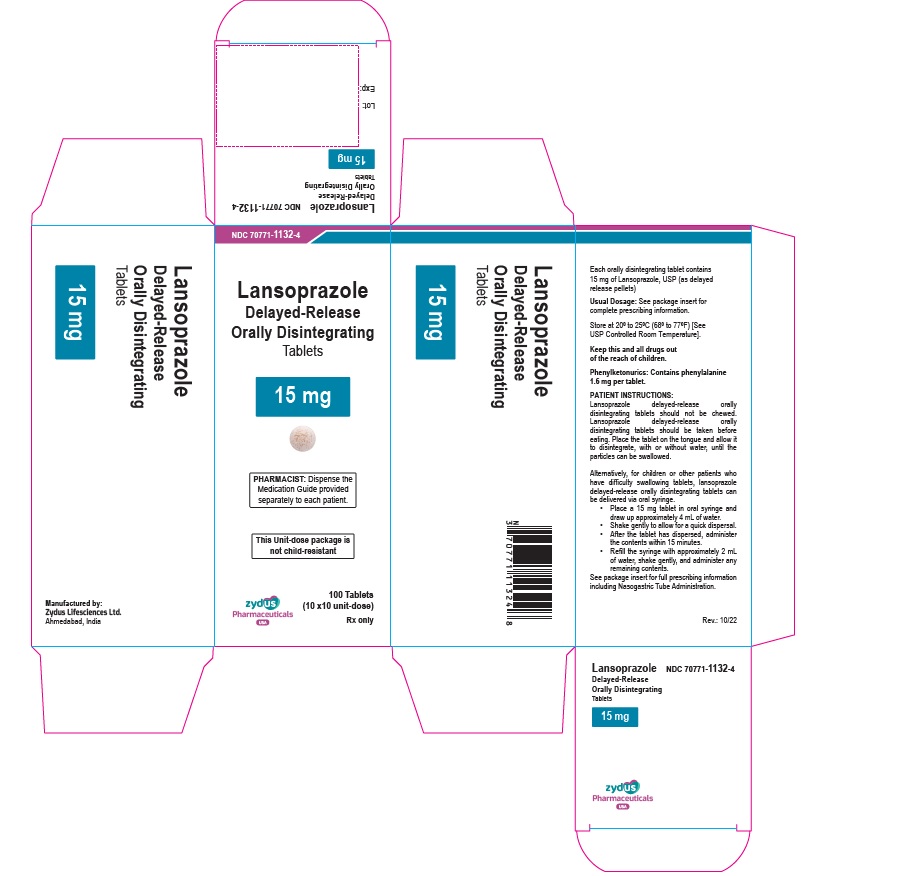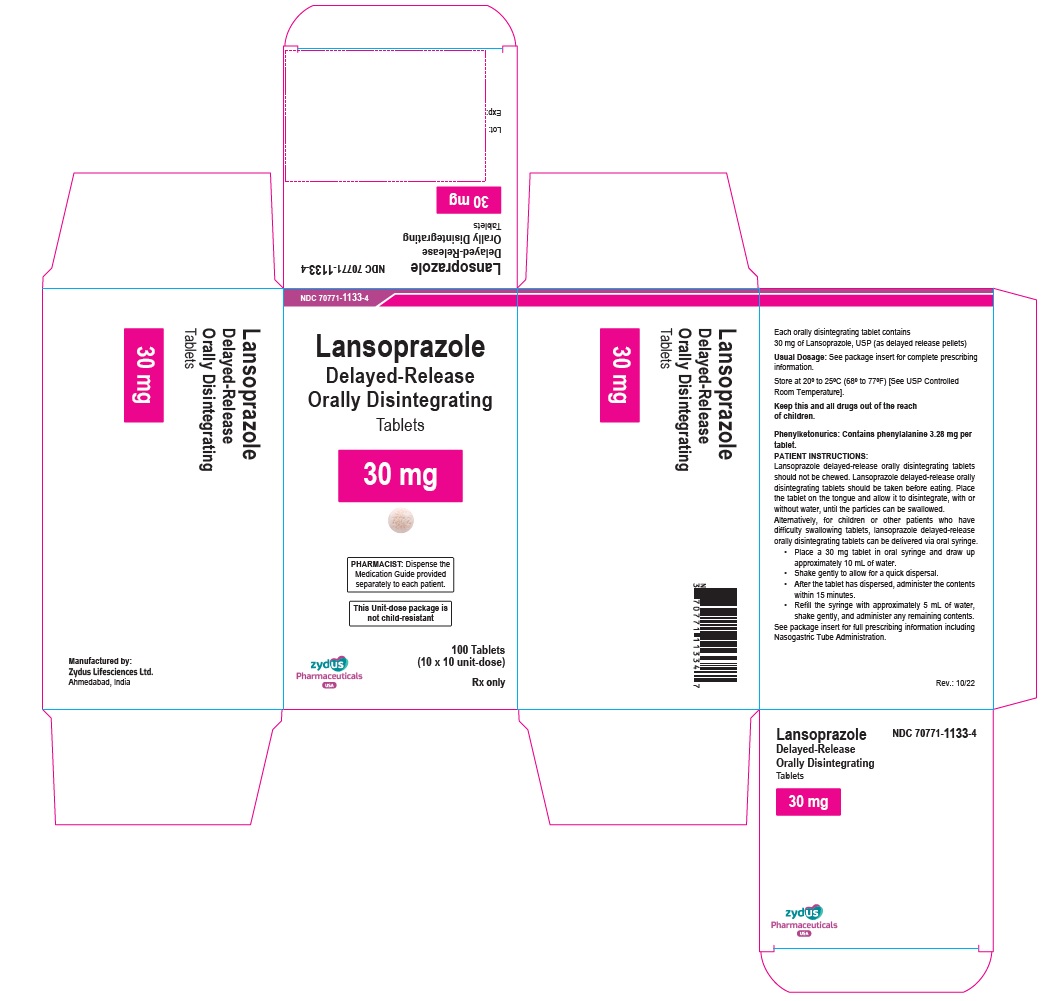 DRUG LABEL: LANSOPRAZOLE
NDC: 70771-1132 | Form: TABLET, ORALLY DISINTEGRATING
Manufacturer: Zydus Lifesciences Limited
Category: prescription | Type: HUMAN PRESCRIPTION DRUG LABEL
Date: 20241130

ACTIVE INGREDIENTS: LANSOPRAZOLE 15 mg/1 1
INACTIVE INGREDIENTS: ANHYDROUS CITRIC ACID; ASPARTAME; CELLULOSE, MICROCRYSTALLINE; CROSPOVIDONE (15 MPA.S AT 5%); FERRIC OXIDE RED; GLYCERYL MONOSTEARATE; HYDROCHLORIC ACID; HYPROMELLOSES; MAGNESIUM CARBONATE; MAGNESIUM STEARATE; MANNITOL; METHACRYLIC ACID AND ETHYL ACRYLATE COPOLYMER; POLYACRYLIC ACID (250000 MW); POLYETHYLENE GLYCOL, UNSPECIFIED; POLYSORBATE 80; SILICON DIOXIDE; SODIUM HYDROXIDE; SODIUM STARCH GLYCOLATE TYPE A POTATO; STARCH, CORN; STRAWBERRY; TALC; TRIETHYL CITRATE; XANTHAN GUM

LANSOPRAZOLE DELAYED-RELEASE ORALLY DISINTEGRATING TABLETS

PACKAGE LABEL.PRINCIPAL DISPLAY PANEL

NDC 70771-1132-4

Lansoprazole Delayed-release Orally Disintegrating Tablets, 15 mg

Rx only

100 Tablets (10 x 10 Unit Dose)

NDC 70771-1133-4

Lansoprazole Delayed-release Orally Disintegrating Tablets, 30 mg

Rx only

100 Tablets (10 x 10 Unit Dose)